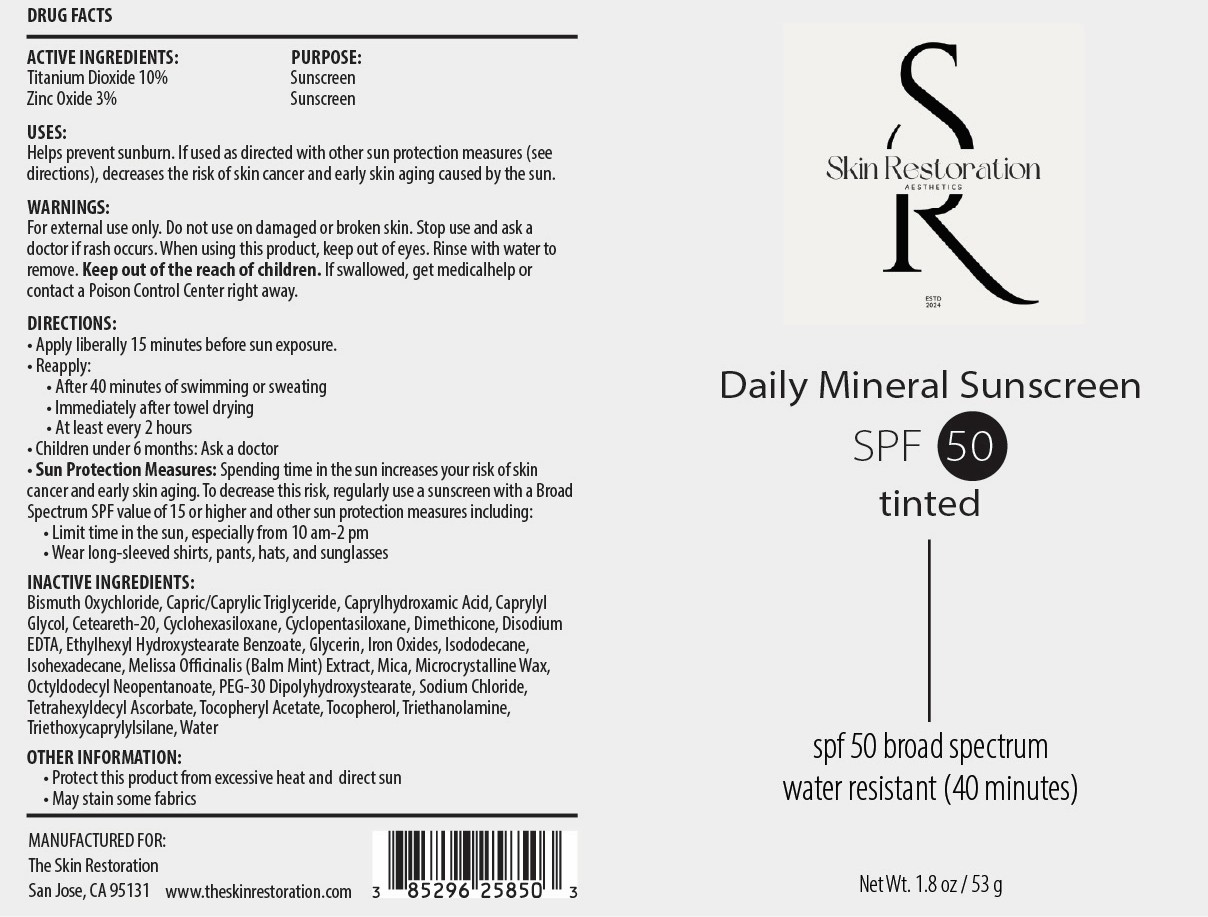 DRUG LABEL: Daily Tinted Mineral SPF
NDC: 85296-258 | Form: CREAM
Manufacturer: Skin Restoration Aesthetics
Category: otc | Type: HUMAN OTC DRUG LABEL
Date: 20251208

ACTIVE INGREDIENTS: TITANIUM DIOXIDE 100 mg/1 g; ZINC OXIDE 30 mg/1 g
INACTIVE INGREDIENTS: MICA; TRIETHANOLAMINE; BISMUTH OXYCHLORIDE; CAPRYLIC/CAPRIC TRIGLYCERIDE; CYCLOPENTASILOXANE; ISOHEXADECANE; CAPRYLHYDROXAMIC ACID; CETEARETH-20; DIMETHICONE; ETHYLHEXYL HYDROXYSTEARATE BENZOATE; CI 77491; EDETATE DISODIUM ANHYDROUS; ISODODECANE; MELISSA OFFICINALIS; PEG-30 DIPOLYHYDROXYSTEARATE; TRIETHOXYCAPRYLYLSILANE; GLYCERIN; WATER; TOCOPHEROL; CAPRYLYL GLYCOL; OCTYLDODECYL NEOPENTANOATE; TETRAHEXYLDECYL ASCORBATE; MICROCRYSTALLINE WAX; SODIUM CHLORIDE; ALPHA-TOCOPHEROL ACETATE; CYCLOHEXASILOXANE; CI 77499; CI 77492

Active Ingredients:

Titanium Dioxide 10%

Zinc Oxide 3%

Purpose:

Sunscreen

Uses:

Helps prevent sunburn. If used as directed with other sun protection measures (see directions), decreases the risk of skin cancer and early skin aging caused by the sun.

Warnings:

For external use only. Do not use on damaged or broken skin. Stop use and ask a doctor if rash occurs. When using this product, keep out of eyes. Rinse with water to remove. Keep out of the reach of children. If swallowed, get medicalhelp or contact a Poison Control Center right away.

Directions:

• Apply liberally 15 minutes before sun exposure. • Reapply: • After 40 minutes of swimming or sweating • Immediately after towel drying • At least every 2 hours • Children under 6 months: Ask a doctor • Sun Protection Measures: Spending time in the sun increases your risk of skin cancer and early skin aging. To decrease this risk, regularly use a sunscreen with a Broad Spectrum SPF value of 15 or higher and other sun protection measures including: • Limit time in the sun, especially from 10 am-2 pm • Wear long-sleeved shirts, pants, hats, and sunglasses

Inactive Ingredients:

Bismuth Oxychloride, Capric/Caprylic Triglyceride, Caprylhydroxamic Acid, Caprylyl Glycol, Ceteareth-20, Cyclohexasiloxane, Cyclopentasiloxane, Dimethicone, Disodium EDTA, Ethylhexyl Hydroxystearate Benzoate, Glycerin, Iron Oxides, Isododecane, Isohexadecane, Melissa Officinalis (Balm Mint) Extract, Mica, Microcrystalline Wax, Octyldodecyl Neopentanoate, PEG-30 Dipolyhydroxystearate, Sodium Chloride, Tetrahexyldecyl Ascorbate, Tocopheryl Acetate, Tocopherol, Triethanolamine, Triethoxycaprylylsilane, Water

Other Information:

• Protect this product from excessive heat and direct sun • May stain some fabrics

Warning:

Keep out of the reach of children